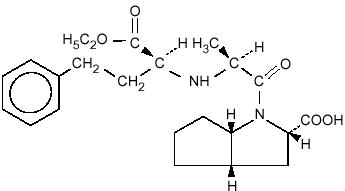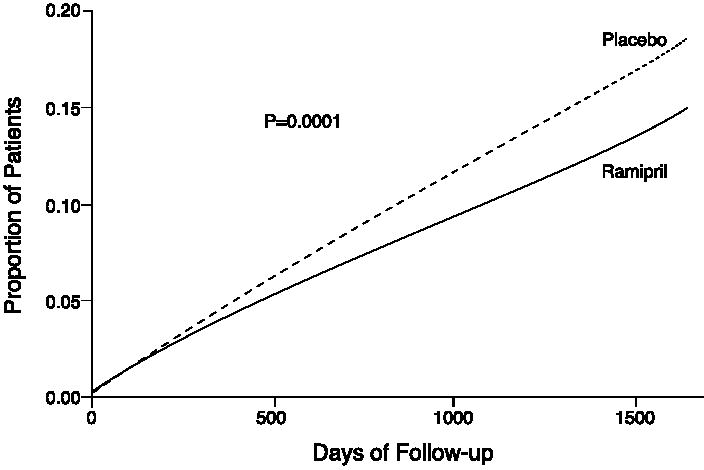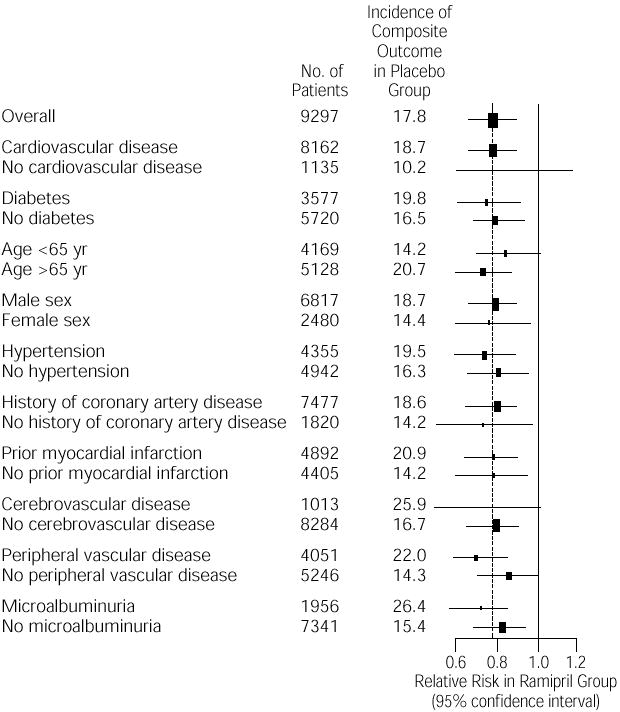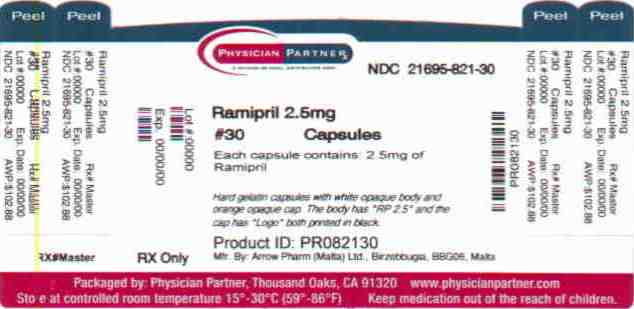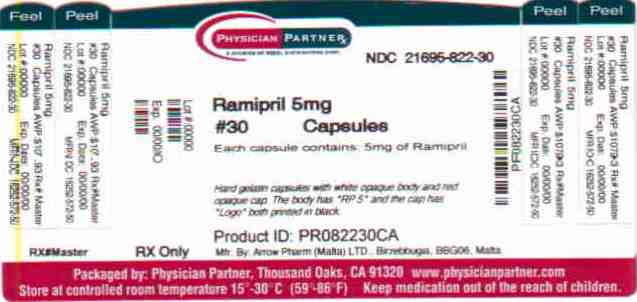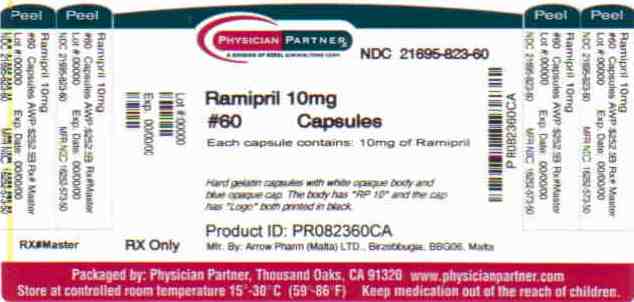 DRUG LABEL: Ramipril
NDC: 21695-821 | Form: CAPSULE
Manufacturer: Rebel Distributors Corp
Category: prescription | Type: HUMAN PRESCRIPTION DRUG LABEL
Date: 20101111

ACTIVE INGREDIENTS: ramipril 2.5 mg/1 1
INACTIVE INGREDIENTS: STARCH, CORN; gelatin; titanium dioxide; D&C YELLOW NO. 10; FD&C RED NO. 40; D&C RED NO. 28; FERRIC OXIDE YELLOW

Ramipril Capsules

BOXED WARNING

When used in pregnancy during the second and third trimesters, ACE inhibitors can cause injury and even death to the developing fetus. When pregnancy is detected, Ramipril should be discontinued as soon as possible. See WARNINGS: Fetal/neonatal Morbidity and Mortality.

DESCRIPTION

Ramipril is a 2-aza-bicyclo [3.3.0]-octane-3-carboxylic acid derivative. It is a white, crystalline substance soluble in polar organic solvents and buffered aqueous solutions. Ramipril melts between 105°C and 112°C.

The CAS Registry Number is 87333-19-5. Ramipril's chemical name is (2S,3aS,6aS)-1[(S)-N-[(S)-1-Carboxy-3-phenylpropyl] alanyl] octahydrocyclopenta [b]pyrrole-2-carboxylic acid, 1-ethyl ester; its structural formula is:

Its molecular formula is C23H32N2O5, and its molecular weight is 416.5.

Ramiprilat, the diacid metabolite of ramipril, is a non-sulfhydryl angiotensin converting enzyme inhibitor. Ramipril is converted to ramiprilat by hepatic cleavage of the ester group.

Ramipril is supplied as hard shell capsules for oral administration containing 1.25 mg, 2.5 mg, 5 mg, and 10 mg of ramipril. The inactive ingredients present are pregelatinized starch NF, gelatin, and titanium dioxide. The 1.25 mg capsule shell contains yellow iron oxide, the 2.5 mg capsule shell contains D&C yellow #10, D&C red #28, FD&C red #40 and yellow iron oxide, the 5 mg capsule shell contains D&C red #28, D&C yellow #10, FD&C blue #1 and FD&C red #40, and the 10 mg capsule shell contains D&C red #28, FD&C blue #1, FD&C red #40 and black iron oxide.

CLINICAL PHARMACOLOGY

Mechanism of Action

Ramipril and ramiprilat inhibit angiotensin-converting enzyme (ACE) in human subjects and animals. ACE is a peptidyl dipeptidase that catalyzes the conversion of angiotensin I to the vasoconstrictor substance, angiotensin II. Angiotensin II also stimulates aldosterone secretion by the adrenal cortex. Inhibition of ACE results in decreased plasma angiotensin II, which leads to decreased vasopressor activity and to decreased aldosterone secretion. The latter decrease may result in a small increase of serum potassium. In hypertensive patients with normal renal function treated with ramipril alone for up to 56 weeks, approximately 4% of patients during the trial had an abnormally high serum potassium and an increase from baseline greater than 0.75 mEq/L, and none of the patients had an abnormally low potassium and a decrease from baseline greater than 0.75 mEq/L. In the same study, approximately 2% of patients treated with ramipril and hydrochlorothiazide for up to 56 weeks had abnormally high potassium values and an increase from baseline of 0.75 mEq/L or greater, and approximately 2% had abnormally low values and decreases from baseline of 0.75 mEq/L or greater. (See PRECAUTIONS.) Removal of angiotensin II negative feedback on renin secretion leads to increased plasma renin activity.

The effect of ramipril on hypertension appears to result at least in part from inhibition of both tissue and circulating ACE activity, thereby reducing angiotensin II formation in tissue and plasma.

ACE is identical to kininase, an enzyme that degrades bradykinin. Whether increased levels of bradykinin, a potent vasodepressor peptide, play a role in the therapeutic effects of ramipril remains to be elucidated.

While the mechanism through which ramipril lowers blood pressure is believed to be primarily suppression of the renin-angiotensin-aldosterone system, ramipril has an antihypertensive effect even in patients with low-renin hypertension. Although ramipril was antihypertensive in all races studied, black hypertensive patients (usually a low-renin hypertensive population) had a smaller average response to monotherapy than non-black patients.

Pharmacokinetics and Metabolism

Following oral administration of ramipril, peak plasma concentrations of ramipril are reached within one hour. The extent of absorption is at least 50–60% and is not significantly influenced by the presence of food in the GI tract, although the rate of absorption is reduced.

In a trial in which subjects received ramipril capsules or the contents of identical capsules dissolved in water, dissolved in apple juice, or suspended in apple sauce, serum ramiprilat levels were essentially unrelated to the use or nonuse of the concomitant liquid or food.

Cleavage of the ester group (primarily in the liver) converts ramipril to its active diacid metabolite, ramiprilat. Peak plasma concentrations of ramiprilat are reached 2–4 hours after drug intake. The serum protein binding of ramipril is about 73% and that of ramiprilat about 56%; in vitro, these percentages are independent of concentration over the range of 0.01 to 10μg/ml.

Ramipril is almost completely metabolized to ramiprilat, which has about 6 times the ACE inhibitory activity of ramipril, and to the diketopiperazine ester, the diketopiperazine acid, and the glucuronides of ramipril and ramiprilat, all of which are inactive. After oral administration of ramipril, about 60% of the parent drug and its metabolites is eliminated in the urine, and about 40% is found in the feces. Drug recovered in the feces may represent both biliary excretion of metabolites and/or unabsorbed drug, however the proportion of a dose eliminated by the bile has not been determined. Less than 2% of the administered dose is recovered in urine as unchanged ramipril.

Blood concentrations of ramipril and ramiprilat increase with increased dose, but are not strictly dose-proportional. The 24-hour AUC for ramiprilat, however, is dose-proportional over the 2.5–20 mg dose range. The absolute bioavailabilities of ramipril and ramiprilat were 28% and 44%, respectively, when 5 mg of oral ramipril was compared with the same dose of ramipril given intravenously.

Plasma concentrations of ramiprilat decline in a triphasic manner (initial rapid decline, apparent elimination phase, terminal elimination phase). The initial rapid decline, which represents distribution of the drug into a large peripheral compartment and subsequent binding to both plasma and tissue ACE, has a half-life of 2–4 hours. Because of its potent binding to ACE and slow dissociation from the enzyme, ramiprilat shows two elimination phases. The apparent elimination phase corresponds to the clearance of free ramiprilat and has a half-life of 9–18 hours. The terminal elimination phase has a prolonged half-life (>50 hours) and probably represents the binding/dissociation kinetics of the ramiprilat/ACE complex. It does not contribute to the accumulation of the drug. After multiple daily doses of ramipril 5–10 mg, the half-life of ramiprilat concentrations within the therapeutic range was 13–17 hours.

After once-daily dosing, steady-state plasma concentrations of ramiprilat are reached by the fourth dose. Steady-state concentrations of ramiprilat are somewhat higher than those seen after the first dose of ramipril, especially at low doses (2.5 mg), but the difference is clinically insignificant.

In patients with creatinine clearance less than 40 ml/min/1.73m^2, peak levels of ramiprilat are approximately doubled, and trough levels may be as much as quintupled. In multiple-dose regimens, the total exposure to ramiprilat (AUC) in these patients is 3–4 times as large as it is in patients with normal renal function who receive similar doses.

The urinary excretion of ramipril, ramiprilat, and their metabolites is reduced in patients with impaired renal function. Compared to normal subjects, patients with creatinine clearance less than 40 ml/min/1.73m^2 had higher peak and trough ramiprilat levels and slightly longer times to peak concentrations. (See DOSAGE AND ADMINISTRATION.)

In patients with impaired liver function, the metabolism of ramipril to ramiprilat appears to be slowed, possibly because of diminished activity of hepatic esterases, and plasma ramipril levels in these patients are increased about 3-fold. Peak concentrations of ramiprilat in these patients, however, are not different from those seen in subjects with normal hepatic function, and the effect of a given dose on plasma ACE activity does not vary with hepatic function.

Pharmacodynamics

Single doses of ramipril of 2.5–20 mg produce approximately 60–80% inhibition of ACE activity 4 hours after dosing with approximately 40–60% inhibition after 24 hours. Multiple oral doses of ramipril of 2.0 mg or more cause plasma ACE activity to fall by more than 90% 4 hours after dosing, with over 80% inhibition of ACE activity remaining 24 hours after dosing. The more prolonged effect of even small multiple doses presumably reflects saturation of ACE binding sites by ramiprilat and relatively slow release from those sites.

Pharmacodynamics and Clinical Effects

Reduction in Risk of Myocardial Infarction, Stroke, and Death from Cardiovascular Causes

The Heart Outcomes Prevention Evaluation study (HOPE study) was a large, multi-center, randomized, placebo controlled,2x2 factorial design, double-blind study conducted in 9,541 patients (4,645 on ramipril) who were 55 years or older and considered at high risk of developing a major cardiovascular event because of a history of coronary artery disease, stroke, peripheral vascular disease, or diabetes that was accompanied by at least one other cardiovascular risk factor (hypertension, elevated total cholesterol levels, low HDL levels, cigarette smoking, or documented microalbuminuria). Patients were either normotensive or under treatment with other antihypertensive agents. Patients were excluded if they had clinical heart failure or were known to have a low ejection fraction (<0.40). This study was designed to examine the long-term (mean of five years) effects of ramipril (10 mg orally once a day) on the combined endpoint of myocardial infarction, stroke or death from cardiovascular causes.

The HOPE study results showed that ramipril (10 mg/day) significantly reduced the rate of myocardial infarction, stroke or death from cardiovascular causes (651/4645 vs. 826/4652, relative risk 0.78), as well as the rates of the 3 components of the combined endpoint.

 | Ramipril | Placebo | Relative Risk
Outcome | (N=4645) | (N=4652) | (95% CI)
 | no. (%) |  | P value
Combined End-point
(MI, stroke, or death from CV cause) | 651 (14.0%) | 826 (17.8%) | 0.78 (0.70–0.86), P=0.0001
Component End-point
Death from Cardiovascular Causes | 282 (6.1%) | 377 (8.1%) | 0.74 (0.64–0.87), P=0.0002
Myocardial infarction | 459 (9.9%) | 570 (12.3%) | 0.80 (0.70–0.90), P=0.0003
Stroke | 156 (3.4%) | 226 (4.9%) | 0.68 (0.56–0.84), P=0.0002
Overall Mortality
(Death from any Cause) | 482 (10.4%) | 569 (12.2%) | 0.84 (0.75–0.95), P=0.005

This effect was evident after about one year of treatment.

Figure 1: Kaplan-Meier Estimates of the composite outcome of MI, Stroke, or Death from CV causes in the Ramipril Group and the Placebo Group. The relative risk of the composite outcomes in the Ramipril Group as compared with the Placebo Group was 0.78% (95% confidence interval, 0.70–0.86).

Ramipril was effective in different demographic subgroups, (i.e., gender, age), subgroups defined by underlying disease (e.g., cardiovascular disease, hypertension), and subgroups defined by concomitant medication. There were insufficient data to determine whether or not ramipril was equally effective in ethnic subgroups.

This study was designed with a prespecified substudy in diabetics with at least one other cardiovascular risk factor. Effects of ramipril on the combined endpoint and its components were similar in diabetics (n=3,577) to those in the overall study population.

 | Ramipril | Placebo | Relative
Outcome | (N=1808) | (N=1769) | Risk Reduction
 | no. (%) |  | (95% CI)
Combined End-point
(MI, stroke, or death from CV cause) | 277 (15.3%) | 351 (19.8%) | 0.25 (0.12–0.36), P=0.0004
Component End-point
Death from Cardiovascular Causes | 112 (6.2%) | 172 (9.7%) | 0.37 (0.21–0.51), P=0.0001
Myocardial infarction | 185 (10.2%) | 229 (12.9%) | 0.22 (0.06–0.36), P=0.01
Stroke | 76 (4.2%) | 108 (6.1%) | 0.33 (0.10–0.50), P=0.007

Figure 2: The Beneficial Effect of Treatment with Ramipril on the Composite Outcome of Myocardial Infarction, Stroke, or Death from Cardiovascular Causes Overall and in Various Subgroups. Cerebrovascular disease was defined as stroke or transient ischemic attacks. The size of each symbol is proportional to the number of patients in each group. The dashed line indicates overall relative risk.

The benefits of ramipril were observed among patients who were taking aspirin or other anti-platelet agents, beta-blockers, and lipid-lowering agents as well as diuretics and calcium channel blockers.

Hypertension

Administration of ramipril to patients with mild to moderate hypertension results in a reduction of both supine and standing blood pressure to about the same extent with no compensatory tachycardia. Symptomatic postural hypotension is infrequent, although it can occur in patients who are salt- and/or volume-depleted. (See WARNINGS.) Use of ramipril in combination with thiazide diuretics gives a blood pressure lowering effect greater than that seen with either agent alone.

In single-dose studies, doses of 5–20 mg of ramipril lowered blood pressure within 1–2 hours, with peak reductions achieved 3–6 hours after dosing. The antihypertensive effect of a single dose persisted for 24 hours. In longer term (4–12 weeks) controlled studies, once-daily doses of 2.5–10 mg were similar in their effect, lowering supine or standing systolic and diastolic blood pressures 24 hours after dosing by about 6/4 mm Hg more than placebo. In comparisons of peak vs. trough effect, the trough effect represented about 50–60% of the peak response. In a titration study comparing divided (bid) vs. qd treatment, the divided regimen was superior, indicating that for some patients the antihypertensive effect with once-daily dosing is not adequately maintained. (See DOSAGE AND ADMINISTRATION.)

In most trials, the antihypertensive effect of ramipril increased during the first several weeks of repeated measurements. The antihypertensive effect of ramipril has been shown to continue during long-term therapy for at least 2 years. Abrupt withdrawal of ramipril has not resulted in a rapid increase in blood pressure.

Ramipril has been compared with other ACE inhibitors, beta-blockers, and thiazide diuretics. It was approximately as effective as other ACE inhibitors and as atenolol. In both caucasians and blacks, hydrochlorothiazide (25 or 50 mg) was significantly more effective than ramipril.

Except for thiazides, no formal interaction studies of ramipril with other antihypertensive agents have been carried out. Limited experience in controlled and uncontrolled trials combining ramipril with a calcium channel blocker, a loop diuretic, or triple therapy (beta-blocker, vasodilator, and a diuretic) indicate no unusual drug-drug interactions. Other ACE inhibitors have had less than additive effects with beta adrenergic blockers, presumably because both drugs lower blood pressure by inhibiting parts of the renin-angiotensin system.

Ramipril was less effective in blacks than in caucasians. The effectiveness of ramipril was not influenced by age, sex, or weight.

In a baseline controlled study of 10 patients with mild essential hypertension, blood pressure reduction was accompanied by a 15% increase in renal blood flow. In healthy volunteers, glomerular filtration rate was unchanged.

INDICATIONS AND USAGE

Reduction in Risk of Myocardial Infarction, Stroke, and Death from Cardiovascular Causes

Ramipril capsules are indicated in patients 55 years or older at high risk of developing a major cardiovascular event because of a history of coronary artery disease, stroke, peripheral vascular disease, or diabetes that is accompanied by at least one other cardiovascular risk factor (hypertension, elevated total cholesterol levels, low HDL levels, cigarette smoking, or documented microalbuminuria), to reduce the risk of myocardial infarction, stroke, or death from cardiovascular causes. Ramipril capsules can be used in addition to other needed treatment (such as antihypertensive, antiplatelet or lipid-lowering therapy).

Hypertension

Ramipril capsules are indicated for the treatment of hypertension. It may be used alone or in combination with thiazide diuretics.

In using ramipril capsules, consideration should be given to the fact that another angiotensin converting enzyme inhibitor, captopril, has caused agranulocytosis, particularly in patients with renal impairment or collagen-vascular disease. Available data are insufficient to show that ramipril capsules do not have a similar risk. (See WARNINGS.)

In considering use of ramipril capsules, it should be noted that in controlled trials ACE inhibitors have an effect on blood pressure that is less in black patients than in non-blacks. In addition, ACE inhibitors (for which adequate data are available) cause a higher rate of angioedema in black than in non-black patients. (See WARNINGS, Angioedema.)

CONTRAINDICATIONS

Ramipril is contraindicated in patients who are hypersensitive to this product or any other angiotensin converting enzyme inhibitor (e.g., a patient who has experienced angioedema during therapy with any other ACE inhibitor).

WARNINGS

Anaphylactoid and Possibly Related Reactions

Presumably because angiotensin-converting enzyme inhibitors affect the metabolism of eicosanoids and polypeptides, including endogenous bradykinin, patients receiving ACE inhibitors (including ramipril) may be subject to a variety of adverse reactions, some of them serious.

Head and Neck Angioedema

Patients with a history of angioedema unrelated to ACE inhibitor therapy may be at increased risk of angioedema while receiving an ACE inhibitor. (See alsoCONTRAINDICATIONS).

Angioedema of the face, extremities, lips, tongue, glottis, and larynx has been reported in patients treated with angiotensin converting enzyme inhibitors. Angioedema associated with laryngeal edema can be fatal. If laryngeal stridor or angioedema of the face, tongue, or glottis occurs, treatment with ramipril should be discontinued and appropriate therapy instituted immediately. Where there is involvement of the tongue, glottis, or larynx, likely to cause airway obstruction, appropriate therapy, e.g., subcutaneous epinephrine solution 1:1,000 (0.3 ml to 0.5 ml) should be promptly administered. (See ADVERSE REACTIONS.)

Intestinal Angioedema

Intestinal angioedema has been reported in patients treated with ACE inhibitors. These patients presented with abdominal pain (with or without nausea or vomiting); in some cases there was no prior history of facial angioedema and C-1 esterase levels were normal. The angioedema was diagnosed by procedures including abdominal CT scan or ultrasound, or at surgery, and symptoms resolved after stopping the ACE inhibitor. Intestinal angioedema should be included in the differential diagnosis of patients on ACE inhibitors presenting with abdominal pain.

In a large U.S. postmarketing study, angioedema (defined as reports of angio, face, larynx, tongue, or throat edema) was reported in 3/1523 (0.20%) of black patients and in 8/8680 (0.09%) of white patients. These rates were not different statistically.

Anaphylactoid reactions during desensitization: Two patients undergoing desensitizing treatment with hymenoptera venom while receiving ACE inhibitors sustained life-threatening anaphylactoid reactions. In the same patients, these reactions were avoided when ACE inhibitors were temporarily withheld, but they reappeared upon inadvertent rechallenge.

Anaphylactoid reactions during membrane exposure: Anaphylactoid reactions have been reported in patients dialyzed with high-flux membranes and treated concomitantly with an ACE inhibitor. Anaphylactoid reactions have also been reported in patients undergoing low-density lipoprotein apheresis with dextran sulfate absorption.

Hypotension

Ramipril can cause symptomatic hypotension, after either the initial dose or a later dose when the dosage has been increased. Like other ACE inhibitors, ramipril has been only rarely associated with hypotension in uncomplicated hypertensive patients. Symptomatic hypotension is most likely to occur in patients who have been volume- and/or salt-depleted as a result of prolonged diuretic therapy, dietary salt restriction, dialysis, diarrhea, or vomiting. Volume and/or salt depletion should be corrected before initiating therapy with ramipril.

In patients with congestive heart failure, with or without associated renal insufficiency, ACE inhibitor therapy may cause excessive hypotension, which may be associated with oliguria or azotemia and, rarely, with acute renal failure and death. In such patients, ramipril therapy should be started under close medical supervision; they should be followed closely for the first 2 weeks of treatment and whenever the dose of ramipril or diuretic is increased.

If hypotension occurs, the patient should be placed in a supine position and, if necessary, treated with intravenous infusion of physiological saline. Ramipril treatment usually can be continued following restoration of blood pressure and volume.

Hepatic Failure

Rarely, ACE inhibitors, including ramipril, have been associated with a syndrome that starts with cholestatic jaundice and progresses to fulminant hepatic necrosis and (sometimes) death. The mechanism of this syndrome is not understood. Patients receiving ACE inhibitors who develop jaundice or marked elevations of hepatic enzymes should discontinue the ACE inhibitor and receive appropriate medical follow-up.

Neutropenia/Agranulocytosis

As with other ACE inhibitors, rarely, a mild – in isolated cases severe – reduction in the red blood cell count and hemoglobin content, white blood cell or platelet count may develop. In isolated cases, agranulocytosis, pancytopenia, and bone marrow depression may occur. Hematological reactions to ACE inhibitors are more likely to occur in patients with collagen vascular disease (e.g. systemic lupus erythematosus, scleroderma) and renal impairment. Monitoring of white blood cell counts should be considered in patients with collagen-vascular disease, especially if the disease is associated with impaired renal function.

Fetal/Neonatal Morbidity and Mortality

ACE inhibitors can cause fetal and neonatal morbidity and death when administered to pregnant women. Several dozen cases have been reported in the world literature. When pregnancy is detected, ACE inhibitors should be discontinued as soon as possible.

The use of ACE inhibitors during the second and third trimesters of pregnancy has been associated with fetal and neonatal injury, including hypotension, neonatal skull hypoplasia, anuria, reversible or irreversible renal failure, and death. Oligohydramnios has also been reported, presumably resulting from decreased fetal renal function; oligohydramnios in this setting has been associated with fetal limb contractures, craniofacial deformation, and hypoplastic lung development. Prematurity, intrauterine growth retardation, and patent ductus arteriosus have also been reported, although it is not clear whether these occurrences were due to the ACE inhibitor exposure.

In a published retrospective epidemiological study, infants whose mothers had taken an ACE inhibitor during their first trimester of pregnancy appeared to have an increased risk of major congenital malformations compared with infants whose mothers had not undergone first trimester exposure to ACE inhibitor drugs. The number of cases of birth defects is small and the findings of this study have not yet been confirmed.

Rarely (probably less often than once in every thousand pregnancies), no alternative to ACE inhibitors will be found. In these rare cases, the mothers should be apprised of the potential hazards to their fetuses, and serial ultrasound examinations should be performed to assess the intraamniotic environment.

If oligohydramnios is observed, ramipril should be discontinued unless it is considered life-saving for the mother. Contraction stress testing (CST), a non-stress test (NST), or biophysical profiling (BPP) may be appropriate, depending upon the week of pregnancy. Patients and physicians should be aware, however, that oligohydramnios may not appear until after the fetus has sustained irreversible injury.

Infants with histories of in utero exposure to ACE inhibitors should be closely observed for hypotension, oliguria, and hyperkalemia. If oliguria occurs, attention should be directed toward support of blood pressure and renal perfusion. Exchange transfusion or dialysis may be required as means of reversing hypotension and/or substituting for disordered renal function. Ramipril which crosses the placenta can be removed from the neonatal circulation by these means, but limited experience has not shown that such removal is central to the treatment of these infants.

No teratogenic effects of ramipril were seen in studies of pregnant rats, rabbits, and cynomolgus monkeys. On a body surface area basis, the doses used were up to approximately 400 times (in rats and monkeys) and 2 times (in rabbits) the recommended human dose.

PRECAUTIONS

Impaired Renal Function: As a consequence of inhibiting the renin-angiotensin-aldosterone system, changes in renal function may be anticipated in susceptible individuals. In patients with severe congestive heart failure whose renal function may depend on the activity of the renin-angiotensin-aldosterone system, treatment with angiotensin converting enzyme inhibitors, including ramipril, may be associated with oliguria and/or progressive azotemia and (rarely) with acute renal failure and/or death.

In hypertensive patients with unilateral or bilateral renal artery stenosis, increases in blood urea nitrogen and serum creatinine may occur. Experience with another angiotensin converting enzyme inhibitor suggests that these increases are usually reversible upon discontinuation of ramipril and/or diuretic therapy. In such patients renal function should be monitored during the first few weeks of therapy. Some hypertensive patients with no apparent pre-existing renal vascular disease have developed increases in blood urea nitrogen and serum creatinine, usually minor and transient, especially when ramipril has been given concomitantly with a diuretic. This is more likely to occur in patients with pre-existing renal impairment. Dosage reduction of ramipril and/or discontinuation of the diuretic may be required.

Evaluation of the hypertensive patient should always include assessment of renal function. (See DOSAGE AND ADMINISTRATION.)

Hyperkalemia: In clinical trials, hyperkalemia (serum potassium greater than 5.7 mEq/L) occurred in approximately 1% of hypertensive patients receiving ramipril. In most cases, these were isolated values, which resolved despite continued therapy. None of these patients was discontinued from the trials because of hyperkalemia. Risk factors for the development of hyperkalemia include renal insufficiency, diabetes mellitus, and the concomitant use of potassium-sparing diuretics, potassium supplements, and/or potassium-containing salt substitutes, which should be used cautiously, if at all, with ramipril. (See Drug Interactions.)

Cough: Presumably due to the inhibition of the degradation of endogenous bradykinin, persistent nonproductive cough has been reported with all ACE inhibitors, always resolving after discontinuation of therapy. ACE inhibitor-induced cough should be considered in the differential diagnosis of cough.

Impaired Liver Function: Since ramipril is primarily metabolized by hepatic esterases to its active moiety, ramiprilat, patients with impaired liver function could develop markedly elevated plasma levels of ramipril. No formal pharmacokinetic studies have been carried out in hypertensive patients with impaired liver function. However, since the renin-angiotensin system may be activated in patients with severe liver cirrhosis and/or ascites, particular caution should be exercised in treating these patients.

Surgery/Anesthesia: In patients undergoing surgery or during anesthesia with agents that produce hypotension, ramipril may block angiotensin II formation that would otherwise occur secondary to compensatory renin release. Hypotension that occurs as a result of this mechanism can be corrected by volume expansion.

Information for Patients

Pregnancy: Female patients of childbearing age should be told about the consequences of exposure to ACE inhibitors during pregnancy. These patients should be asked to report pregnancies to their physicians as soon as possible.

Angioedema: Angioedema, including laryngeal edema, can occur with treatment with ACE inhibitors, especially following the first dose. Patients should be so advised and told to report immediately any signs or symptoms suggesting angioedema (swelling of face, eyes, lips, or tongue, or difficulty in breathing) and to take no more drug until they have consulted with the prescribing physician.

Symptomatic Hypotension: Patients should be cautioned that lightheadedness can occur, especially during the first days of therapy, and it should be reported. Patients should be told that if syncope occurs, ramipril should be discontinued until the physician has been consulted.

All patients should be cautioned that inadequate fluid intake or excessive perspiration, diarrhea, or vomiting can lead to an excessive fall in blood pressure, with the same consequences of lightheadedness and possible syncope.

Hyperkalemia: Patients should be told not to use salt substitutes containing potassium without consulting their physician.

Neutropenia: Patients should be told to promptly report any indication of infection (e.g., sore throat, fever), which could be a sign of neutropenia.

Drug Interactions

Gold: Nitritoid reactions (symptoms include facial flushing, nausea, vomiting and hypotension) have been reported rarely in patients on therapy with injectable gold (sodium aurothiomalate) and concomitant ACE inhibitor therapy including ramipril.

With nonsteroidal anti-inflammatory agents: Rarely, concomitant treatment with ACE inhibitors and nonsteroidal anti-inflammatory agents have been associated with worsening of renal failure and an increase in serum potassium.

With diuretics: Patients on diuretics, especially those in whom diuretic therapy was recently instituted, may occasionally experience an excessive reduction of blood pressure after initiation of therapy with ramipril. The possibility of hypotensive effects with ramipril can be minimized by either discontinuing the diuretic or increasing the salt intake prior to initiation of treatment with ramipril. If this is not possible, the starting dose should be reduced. (See DOSAGE AND ADMINISTRATION.)

With potassium supplements and potassium-sparing diuretics: Ramipril can attenuate potassium loss caused by thiazide diuretics. Potassium-sparing diuretics (spironolactone, amiloride, triamterene, and others) or potassium supplements can increase the risk of hyperkalemia. Therefore, if concomitant use of such agents is indicated, they should be given with caution, and the patient's serum potassium should be monitored frequently.

With lithium: Increased serum lithium levels and symptoms of lithium toxicity have been reported in patients receiving ACE inhibitors during therapy with lithium. These drugs should be coadministered with caution, and frequent monitoring of serum lithium levels is recommended. If a diuretic is also used, the risk of lithium toxicity may be increased.

Other: Neither ramipril nor its metabolites have been found to interact with food, digoxin, antacid, furosemide, cimetidine, indomethacin, and simvastatin. The combination of ramipril and propranolol showed no adverse effects on dynamic parameters (blood pressure and heart rate). The co-administration of ramipril and warfarin did not adversely affect the anticoagulant effects of the latter drug. Additionally, co-administration of ramipril with phenprocoumon did not affect minimum phenprocoumon levels or interfere with the subjects' state of anti-coagulation.

Carcinogenesis, Mutagenesis, Impairment of Fertility

No evidence of a tumorigenic effect was found when ramipril was given by gavage to rats for up to 24 months at doses of up to 500 mg/kg/day or to mice for up to 18 months at doses of up to 1000 mg/kg/day. (For either species, these doses are about 200 times the maximum recommended human dose when compared on the basis of body surface area.) No mutagenic activity was detected in the Ames test in bacteria, the micronucleus test in mice, unscheduled DNA synthesis in a human cell line, or a forward gene-mutation assay in a Chinese hamster ovary cell line. Several metabolites and degradation products of ramipril were also negative in the Ames test. A study in rats with dosages as great as 500 mg/kg/day did not produce adverse effects on fertility.

Pregnancy

Pregnancy Categories C (first trimester) and D (second and third trimesters). See WARNINGS: Fetal/Neonatal Morbidity and Mortality.

Nursing Mothers

Ingestion of single 10 mg oral dose of ramipril resulted in undetectable amounts of ramipril and its metabolites in breast milk. However, because multiple doses may produce low milk concentrations that are not predictable from single doses, women receiving ramipril should not breast feed.

Geriatric Use

Of the total number of patients who received ramipril in US clinical studies of ramipril 11.0% were 65 and over while 0.2% were 75 and over. No overall differences in effectiveness or safety were observed between these patients and younger patients, and other reported clinical experience has not identified differences in responses between the elderly and younger patients, but greater sensitivity of some older individuals cannot be ruled out.

One pharmacokinetic study conducted in hospitalized elderly patients indicated that peak ramiprilat levels and area under the plasma concentration time curve (AUC) for ramiprilat are higher in older patients.

Pediatric Use

Safety and effectiveness in pediatric patients have not been established. Irreversible kidney damage has been observed in very young rats given a single dose of ramipril.

ADVERSE REACTIONS

Hypertension

Ramipril has been evaluated for safety in over 4,000 patients with hypertension; of these, 1,230 patients were studied in US controlled trials, and 1,107 were studied in foreign controlled trials. Almost 700 of these patients were treated for at least one year. The overall incidence of reported adverse events was similar in ramipril and placebo patients. The most frequent clinical side effects (possibly or probably related to study drug) reported by patients receiving ramipril in US placebo-controlled trials were: headache (5.4%), "dizziness″ (2.2%) and fatigue or asthenia (2.0%), but only the last was more common in ramipril patients than in patients given placebo. Generally, the side effects were mild and transient, and there was no relation to total dosage within the range of 1.25 to 20 mg. Discontinuation of therapy because of a side effect was required in approximately 3% of US patients treated with ramipril. The most common reasons for discontinuation were: cough (1.0%), "dizziness″ (0.5%), and impotence (0.4%).

Of observed side effects considered possibly or probably related to study drug that occurred in US placebo-controlled trials in more than 1% of patients treated with ramipril, only asthenia (fatigue) was more common on ramipril than placebo (2% vs. 1%).

PATIENTS IN US PLACEBO CONTROLLED STUDIES
 | Ramipril |  |  | Placebo
 | (n=651) |  |  | (n=286)
 | n | % |  | n | %
Asthenia (Fatigue) | 13 | 2 |  | 2 | 1

In placebo-controlled trials, there was also an excess of upper respiratory infection and flu syndrome in the ramipril group, not attributed at that time to ramipril. As these studies were carried out before the relationship of cough to ACE inhibitors was recognized, some of these events may represent ramipril-induced cough. In a later 1-year study, increased cough was seen in almost 12% of ramipril patients, with about 4% of patients requiring discontinuation of treatment.

Percentage of Patients with Adverse Events Possibly/ Probably Related to Study Drug

HOPE Study:

Safety data in the HOPE trial were collected as reasons for discontinuation or temporary interruption of treatment. The rate of angioedema was the same as in previous clinical trials (see WARNINGS).

 | Ramipril | Placebo
 | (n=4645) | (n=4652)
 | % | %
Discontinuation at any time | 34 | 32
Permanent discontinuation | 29 | 28
Reasons for stopping Cough | 7 | 2
Hypotension or Dizziness | 1.9 | 1.5
Angioedema | 0.3 | 0.1

Other adverse experiences reported in controlled clinical trials (in less than 1% of ramipril patients), or rarer events seen in postmarketing experience, include the following (in some, a causal relationship to drug use is uncertain):

Body As a Whole: Anaphylactoid reactions. (See WARNINGS.)

Cardiovascular: Symptomatic hypotension (reported in 0.5% of patients in US trials) (See WARNINGS and PRECAUTIONS), syncope and palpitations.

Hematologic: Pancytopenia, hemolytic anemia and thrombocytopenia.

Renal: Some hypertensive patients with no apparent pre-existing renal disease have developed minor, usually transient, increases in blood urea nitrogen and serum creatinine when taking ramipril, particularly when ramipril was given concomitantly with a diuretic. (See WARNINGS.) Acute renal failure.

Angioneurotic Edema: Angioneurotic edema has been reported in 0.3% of patients in US clinical trials. (See WARNINGS.)

Gastrointestinal: Hepatic failure, hepatitis, jaundice, pancreatitis, abdominal pain (sometimes with enzyme changes suggesting pancreatitis), anorexia, constipation, diarrhea, dry mouth, dyspepsia, dysphagia, gastroenteritis, increased salivation and taste disturbance.

Dermatologic: Apparent hypersensitivity reactions (manifested by urticaria, pruritus, or rash, with or without fever), photosensitivity, purpura, onycholysis, pemphigus, pemphigoid, erythema multiforme, toxic epidermal necrolysis, and Stevens-Johnson syndrome.

Neurologic and Psychiatric: Anxiety, amnesia, convulsions, depression, hearing loss, insomnia, nervousness, neuralgia, neuropathy, paresthesia, somnolence, tinnitus, tremor, vertigo, and vision disturbances.

Miscellaneous: As with other ACE inhibitors, a symptom complex has been reported which may include a positive ANA, an elevated erythrocyte sedimentation rate, arthralgia/arthritis, myalgia, fever, vasculitis, eosinophilia, photosensitivity, rash and other dermatologic manifestations. Additionally, as with other ACE inhibitors, eosinophilic pneumonitis has been reported.

Fetal/Neonatal Morbidity and Mortality. See WARNINGS: Fetal/Neonatal Morbidity and Mortality.

Other: Arthralgia, arthritis, dyspnea, edema, epistaxis, impotence, increased sweating, malaise, myalgia, and weight gain.

Post-Marketing Experience: In addition to adverse events reported from clinical trials, there have been rare reports of hypoglycemia reported during ramipril therapy when given to patients concomitantly taking oral hypoglycemic agents or insulin. The causal relationship is unknown.

Clinical Laboratory Test Findings:

Creatinine and Blood Urea Nitrogen: Increases in creatinine levels occurred in 1.2% of patients receiving ramipril alone, and in 1.5% of patients receiving ramipril and a diuretic. Increases in blood urea nitrogen levels occurred in 0.5% of patients receiving ramipril alone and in 3% of patients receiving ramipril with a diuretic. None of these increases required discontinuation of treatment. Increases in these laboratory values are more likely to occur in patients with renal insufficiency or those pretreated with a diuretic and, based on experience with other ACE inhibitors, would be expected to be especially likely in patients with renal artery stenosis. (See WARNINGS and PRECAUTIONS.) Since ramipril decreases aldosterone secretion, elevation of serum potassium can occur. Potassium supplements and potassium-sparing diuretics should be given with caution, and the patient's serum potassium should be monitored frequently. (See WARNINGS and PRECAUTIONS.)

Hemoglobin and Hematocrit: Decreases in hemoglobin or hematocrit (a low value and a decrease of 5 g/dl or 5% respectively) were rare, occurring in 0.4% of patients receiving ramipril alone and in 1.5% of patients receiving ramipril plus a diuretic. No US patients discontinued treatment because of decreases in hemoglobin or hematocrit.

Other (causal relationships unknown): Clinically important changes in standard laboratory tests were rarely associated with ramipril administration. Elevations of liver enzymes, serum bilirubin, uric acid, and blood glucose have been reported, as have cases of hyponatremia and scattered incidents of leukopenia, eosinophilia, and proteinuria. In US trials, less than 0.2% of patients discontinued treatment for laboratory abnormalities; all of these were cases of proteinuria or abnormal liver-function tests.

OVERDOSAGE

Single oral doses in rats and mice of 10–11 g/kg resulted in significant lethality. In dogs, oral doses as high as 1 g/kg induced only mild gastrointestinal distress. Limited data on human overdosage are available. The most likely clinical manifestations would be symptoms attributable to hypotension.

Laboratory determinations of serum levels of ramipril and its metabolites are not widely available, and such determinations have, in any event, no established role in the management of ramipril overdose.

No data are available to suggest physiological maneuvers (e.g., maneuvers to change the pH of the urine) that might accelerate elimination of ramipril and its metabolites. Similarly, it is not known which, if any, of these substances can be usefully removed from the body by hemodialysis.

Angiotensin II could presumably serve as a specific antagonist-antidote in the setting of ramipril overdose, but angiotensin II is essentially unavailable outside of scattered research facilities. Because the hypotensive effect of ramipril is achieved through vasodilation and effective hypovolemia, it is reasonable to treat ramipril overdose by infusion of normal saline solution.

DOSAGE AND ADMINISTRATION

Blood pressure decreases associated with any dose of ramipril capsules depend, in part, on the presence or absence of volume depletion (e.g., past and current diuretic use) or the presence or absence of renal artery stenosis. If such circumstances are suspected to be present, the initial starting dose should be 1.25 mg once daily.

Reduction in Risk of Myocardial Infarction, Stroke, and Death from Cardiovascular Causes

Ramipril capsules should be given at an initial dose of 2.5 mg, once a day for 1 week, 5 mg, once a day for the next 3 weeks, and then increased as tolerated, to a maintenance dose of 10 mg, once a day. If the patient is hypertensive or recently post myocardial infarction, it can also be given as a divided dose.

Hypertension

The recommended initial dose for patients not receiving a diuretic is 2.5 mg once a day. Dosage should be adjusted according to the blood pressure response. The usual maintenance dosage range is 2.5 to 20 mg per day administered as a single dose or in two equally divided doses. In some patients treated once daily, the antihypertensive effect may diminish toward the end of the dosing interval. In such patients, an increase in dosage or twice daily administration should be considered. If blood pressure is not controlled with ramipril capsules alone, a diuretic can be added.

After the initial dose of ramipril capsules, the patient should be observed under medical supervision for at least two hours and until blood pressure has stabilized for at least an additional hour. (See WARNINGS and PRECAUTIONS, Drug Interactions.) If possible, the dose of any concomitant diuretic should be reduced which may diminish the likelihood of hypotension. The appearance of hypotension after the initial dose of ramipril capsules does not preclude subsequent careful dose titration with the drug, following effective management of the hypotension.

The ramipril capsule is usually swallowed whole. The ramipril capsule can also be opened and the contents sprinkled on a small amount (about 4 oz.) of apple sauce or mixed in 4 oz. (120 ml) of water or apple juice. To be sure that ramipril is not lost when such a mixture is used, the mixture should be consumed in its entirety. The described mixtures can be pre-prepared and stored for up to 24 hours at room temperature or up to 48 hours under refrigeration.

Concomitant administration of ramipril capsules with potassium supplements, potassium salt substitutes, or potassium-sparing diuretics can lead to increases of serum potassium. (See PRECAUTIONS.)

In patients who are currently being treated with a diuretic, symptomatic hypotension occasionally can occur following the initial dose of ramipril capsules. To reduce the likelihood of hypotension, the diuretic should, if possible, be discontinued two to three days prior to beginning therapy with ramipril capsules. (See WARNINGS.) Then, if blood pressure is not controlled with ramipril capsules alone, diuretic therapy should be resumed.

If the diuretic cannot be discontinued, an initial dose of 1.25 mg ramipril capsules should be used to avoid excess hypotension.

Dosage Adjustment in Renal Impairment

In patients with creatinine clearance <40 ml/min/1.73m^2 (serum creatinine approximately >2.5 mg/dl) doses only 25% of those normally used should be expected to induce full therapeutic levels of ramiprilat. (See CLINICAL PHARMACOLOGY.)

Hypertension: For patients with hypertension and renal impairment, the recommended initial dose is 1.25 mg ramipril capsules once daily. Dosage may be titrated upward until blood pressure is controlled or to a maximum total daily dose of 5 mg.

HOW SUPPLIED

Ramipril is available in potencies of 1.25 mg, 2.5 mg, 5 mg, and 10 mg in hard gelatin capsules.

Ramipril 2.5 mg capsules are supplied as hard gelatin capsules with white opaque body and orange opaque cap. The body has “RP 2.5" and the cap has “>” both printed in black:
bottles of 30 (NDC 21695-821-30).

Ramipril 5 mg capsules are supplied as hard gelatin capsules with white opaque body and red opaque cap. The body has “RP 5" and the cap has “>” both printed in black:
bottles of 30 (NDC 21695-822-30).

Ramipril 10 mg capsules are supplied hard gelatin capsules with white opaque body and blue opaque cap. The body has “RP 10" and the cap has “>” both printed in black:
bottles of 30 (NDC 21695-823-30).

Dispense in well-closed container with safety closure.
Store at controlled room temperature, 20 to 25oC (68 to 77oF) with excursions permitted between 15 to 30oC (59 to 86oF). (See USP).

Manufactured for: Cobalt Laboratories, Bonita Springs, Florida, U.S.A., 34134

Item Number: LFT0129AB
Date: May 2009

Repackaged by: Rebel Distributors Corp, Thousand Oaks, CA 91320

PACKAGE LABEL.PRINCIPAL DISPLAY PANEL SECTION

Representative Sample of Label - 2.5 mg

Rx only

NDC 21695-821-30

RAMIPRIL CAPSULES

2.5 mg

30 capsules

Rebel Distributors

PACKAGE LABEL.PRINCIPAL DISPLAY PANEL SECTION

Representative Sample of Label - 5 mg

Rx only

NDC 21695-822-30

RAMIPRIL CAPSULES

5 mg

30 capsules

Rebel Distributors

PACKAGE LABEL.PRINCIPAL DISPLAY PANEL SECTION

Representative Sample of Label - 10 mg

Rx only

NDC 21695-823-30

RAMIPRIL CAPSULES

10 mg

30 capsules

Rebel Distributors